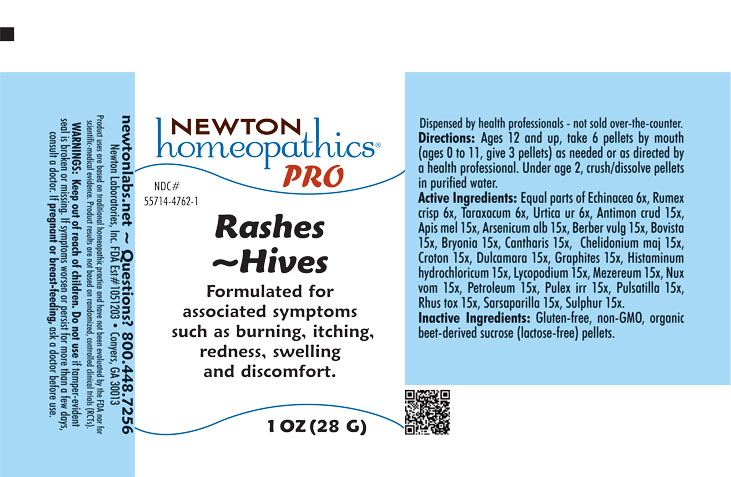 DRUG LABEL: Rashes-Hives
NDC: 55714-4762 | Form: PELLET
Manufacturer: Newton Laboratories, Inc.
Category: homeopathic | Type: HUMAN OTC DRUG LABEL
Date: 20250929

ACTIVE INGREDIENTS: TARAXACUM OFFICINALE 6 [hp_X]/1 g; URTICA URENS 6 [hp_X]/1 g; SMILAX ORNATA ROOT 15 [hp_X]/1 g; ANTIMONY TRISULFIDE 15 [hp_X]/1 g; APIS MELLIFERA 15 [hp_X]/1 g; ARSENIC TRIOXIDE 15 [hp_X]/1 g; BERBERIS VULGARIS ROOT BARK 15 [hp_X]/1 g; LYCOPERDON UTRIFORME FRUITING BODY 15 [hp_X]/1 g; BRYONIA ALBA ROOT 15 [hp_X]/1 g; LYTTA VESICATORIA 15 [hp_X]/1 g; CHELIDONIUM MAJUS 15 [hp_X]/1 g; CROTON TIGLIUM SEED 15 [hp_X]/1 g; SOLANUM DULCAMARA TOP 15 [hp_X]/1 g; GRAPHITE 15 [hp_X]/1 g; HISTAMINE DIHYDROCHLORIDE 15 [hp_X]/1 g; LYCOPODIUM CLAVATUM SPORE 15 [hp_X]/1 g; DAPHNE MEZEREUM BARK 15 [hp_X]/1 g; STRYCHNOS NUX-VOMICA SEED 15 [hp_X]/1 g; KEROSENE 15 [hp_X]/1 g; PULEX IRRITANS 15 [hp_X]/1 g; ANEMONE PULSATILLA 15 [hp_X]/1 g; TOXICODENDRON PUBESCENS LEAF 15 [hp_X]/1 g; SULFUR 15 [hp_X]/1 g; ECHINACEA, UNSPECIFIED 6 [hp_X]/1 g; RUMEX CRISPUS ROOT 6 [hp_X]/1 g
INACTIVE INGREDIENTS: SUCROSE

Rashes 4762P

INDICATIONS & USAGE SECTION

Formulated for associated symptoms such as burning, itching, redness, swelling and discomfort.

DOSAGE & ADMINISTRATION SECTION

Directions: Ages 12 and up, take 6 pellets by mouth (ages 0 to 11, give 3 pellets) as needed or as directed by a health professional. Under age 2, crush/dissolve pellets in purified water.

OTC - ACTIVE INGREDIENT SECTION

Equal parts of Echinacea 6x, Rumex crisp. 6x, Taraxacum 6x, Urtica ur. 6x. Antimon. crud. 15x, Apis mel. 15x, Arsenicum alb. 15x, Berber. vulg. 15x, Bovista 15x, Bryonia 15x, Cantharis 15x, Chelidonium majus 15x, Croton 15x, Dulcamara 15x, Graphites 15x, Histaminum hydrochloricum 15x, Lycopodium 15x, Mezereum 15x, Nux vom. 15x, Petroleum 15x, Pulex irritans 15x, Pulsatilla 15x, Rhus toxicodendron 15x, Sarsaparilla 15x, Sulphur 15x,

OTC - PURPOSE SECTION

Formulated for associated symptoms such as burning, itching, redness, swelling and discomfort.

INACTIVE INGREDIENT SECTION

Inactive Ingredients: Gluten-free, non-GMO, beet-derived sucrose pellets.

QUESTIONS SECTION

newtonlabs.net – Questions? 800.448.7256

Newton Laboratories, Inc. FDA Est # 1051203 - Conyers, GA 30013

WARNINGS SECTION

WARNINGS: Keep out of reach of children. Do not use if tamper-evident seal is broken or missing. If symptoms worsen or persist for more than a few days, consult a doctor. If pregnant or breast-feeding, ask a doctor before use.

OTC - PREGNANCY OR BREAST FEEDING SECTION

If pregnant or breast-feeding, ask a doctor before use.

OTC - KEEP OUT OF REACH OF CHILDREN SECTION

Keep out of reach of children.